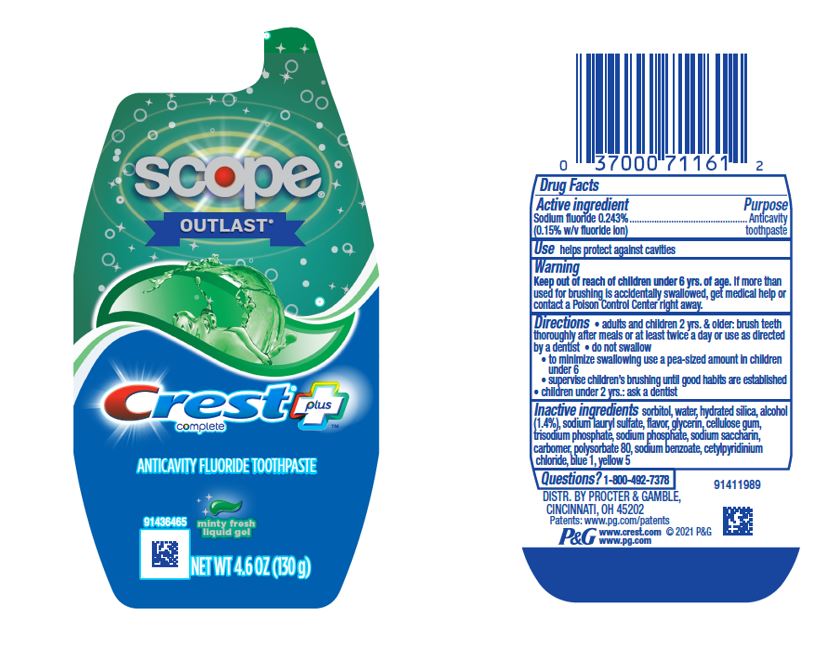 DRUG LABEL: Crest Complete Plus
NDC: 37000-983 | Form: GEL, DENTIFRICE
Manufacturer: The Procter & Gamble Manufacturing Company
Category: otc | Type: HUMAN OTC DRUG LABEL
Date: 20250225

ACTIVE INGREDIENTS: SODIUM FLUORIDE 1.5 mg/1 g
INACTIVE INGREDIENTS: WATER; HYDRATED SILICA; SODIUM PHOSPHATE, TRIBASIC, ANHYDROUS; SODIUM PHOSPHATE; CARBOXYPOLYMETHYLENE; SODIUM LAURYL SULFATE; ALCOHOL; CARBOXYMETHYLCELLULOSE SODIUM; SACCHARIN SODIUM; GLYCERIN; POLYSORBATE 80; SODIUM BENZOATE; CETYLPYRIDINIUM CHLORIDE; FD&C BLUE NO. 1; FD&C YELLOW NO. 5; SORBITOL

Crest Complete Plus Scope Outlast Liquid Gel

Drug Facts

Active ingredient

Sodium fluoride 0.243%

(0.15% w/v fluoride ion)

Purpose

Anticavity toothpaste

Use

helps protect against cavities

Warnings

Keep out of reach of children under 6 yrs. of age. If more than used for brushing is accidentally swallowed, get medical help or contact a Poison Control Center right away.

Directions

- adults and children 2 yrs. & older: brush teeth thoroughly after meals or at least twice a day or use as directed by a dentist
  - do not swallow
  - to minimize swallowing use a pea-sized amount in children under 6
  - supervise children's brushing until good habits are established
- children under 2 yrs.: ask a dentist

Inactive ingredients

sorbitol, water, hydrated silica, alcohol (1.4%), sodium lauryl sulfate, flavor, glycerin, cellulose gum, trisodium phosphate, sodium phosphate, sodium saccharin, carbomer, polysorbate 80, sodium benzoate, cetylpyridinium chloride, blue 1, yellow 5

Questions?

1-800-492-7378

Dist. by Procter & Gamble, Cincinnati, OH 45202

PRINCIPAL DISPLAY PANEL - 130 g Bottle Label

scope®

OUTLAST®

Crest® plus
complete

ANTICAVITY FLUORIDE TOOTHPASTE
minty fresh
liquid gel

NET WT 4.6 OZ (130 g)